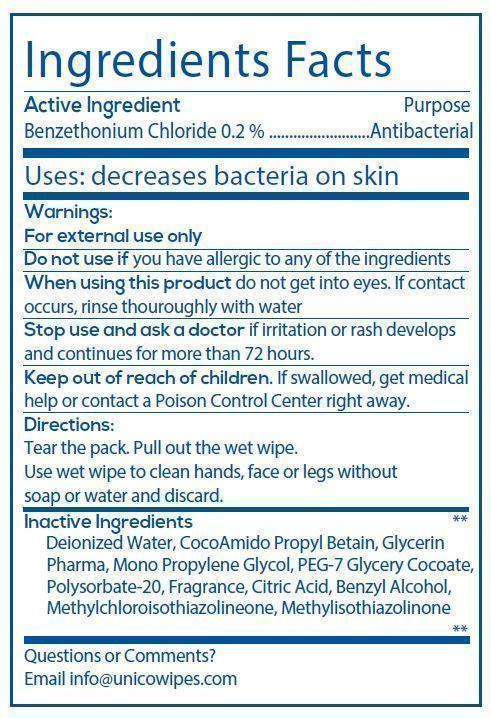 DRUG LABEL: Unicowipes
NDC: 69652-000 | Form: CLOTH
Manufacturer: Sabah Gida Saglik Temizlik Urunleri Dolum Ve Ambalaj Sana
Category: otc | Type: HUMAN OTC DRUG LABEL
Date: 20150423

ACTIVE INGREDIENTS: BENZETHONIUM CHLORIDE 0.001 mg/1 1
INACTIVE INGREDIENTS: WATER; COCAMIDOPROPYL BETAINE; GLYCERIN; PROPYLENE GLYCOL; PEG-7 GLYCERYL COCOATE; POLYSORBATE 20; CITRIC ACID MONOHYDRATE; BENZYL ALCOHOL; METHYLCHLOROISOTHIAZOLINONE; METHYLISOTHIAZOLINONE

Active Ingredient Purpose

Benzethonium Chloride 0.2% ....................... Antibacterial

PURPOSE

Uses: decreases bacteria on skin

Keep out of reach of children. If swallowed, get medical help or contact a Poison Control Center right away.

INDICATIONS AND USAGE

Unicowipes

Warnings:

For external use only

Do not use if you have allergic to any of the ingredients

When using this product do not get into eyes. If contact occurs, rinse thoroughly with water

Stop use and ask a doctor if irritation or rash develops and continues for more than 72 hours

Directions:

Tear the pack. Pull out the wet wipe.

Use wet wipe to clean hands, face or legs without soap or water and discard.

Inactive Ingredients

deionized water, cocoamido propyl betain, glycerin pharma, mono propylene glycol, PEG-7 glycery cocoate, polysorbate-20, fragrance, citric acid, benzyl alcohol, methylchloroisothiazolinone, methylisothiazolinone.